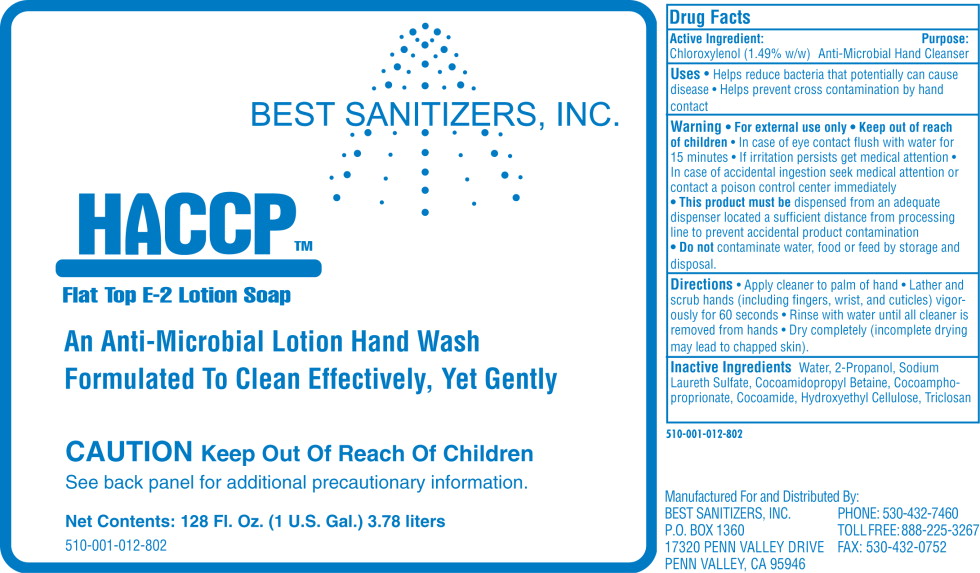 DRUG LABEL: HACCP Flat Top E-2
NDC: 59900-510 | Form: LIQUID
Manufacturer: Best Sanitizers Inc.
Category: otc | Type: HUMAN OTC DRUG LABEL
Date: 20100903

ACTIVE INGREDIENTS: chloroxylenol 15.75 g/1000 mL
INACTIVE INGREDIENTS: water; sodium laureth sulfate; cocamidopropyl betaine; hydroxyethyl cellulose (2000 CPS at 1%); isopropyl alcohol; coco diethanolamide; triclosan

HACCP Flat Top E-2 Lotion Soap

Active Ingredient:

Chloroxylenol (1.49% w/w)

Purpose:

Anti-Microbial Hand Cleanser

Uses

- Helps reduce bacteria that potentially can cause disease
- Helps prevent cross contamination by hand contact

Warnings

- For external use only.

- Keep out of reach of children.
- In case of eye contact flush with water for 15 minutes. • If irritation persists, get medical attention. • In case of accidental ingestion, seek medical attention or contact a poison control center immediately.
- This product must be dispensed from an adequate dispenser located a sufficient distance from processing line to prevent accidental product contamination.
- Do not contaminate water, food or feed by storage and disposal.

Directions

- Apply cleaner to palm of hand
- Lather and scrub hands (including fingers, wrist, and cuticles) vigorously for 60 seconds
- Rinse with water until all cleaner is removed from hands
- Dry completely (incomplete drying may lead to chapped skin).

Inactive Ingredients

Water, 2-Propanol, Sodium Laureth Sulfate, Cocoamidopropyl Betaine, Cocoamphoproprionate,
Cocoamide, Hydroxyethyl Cellulose, Triclosan

510-001-012-802

Manufactured For and Distributed By:
BEST SANITIZERS, INC.
P.O. BOX 1360
17320 PENN VALLEY DRIVE
PENN VALLEY, CA 95946
PHONE: 530-432-7460
TOLL FREE: 888-225-3267
PHONE: 530-432-0752

Principal Display Panel – Bottle Label

Bottle Label:

BEST SANITIZERS, INC.

HACCP

Flat Top E-2 Lotion Soap

An Anti-Microbial Lotion Hand Wash
Formulated To Clean Effectively, Yet Gently

CAUTION Keep Out Of Reach Of Children

See back panel for additional precautionary information.